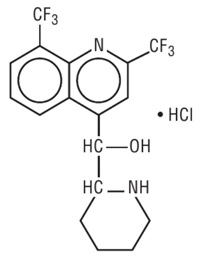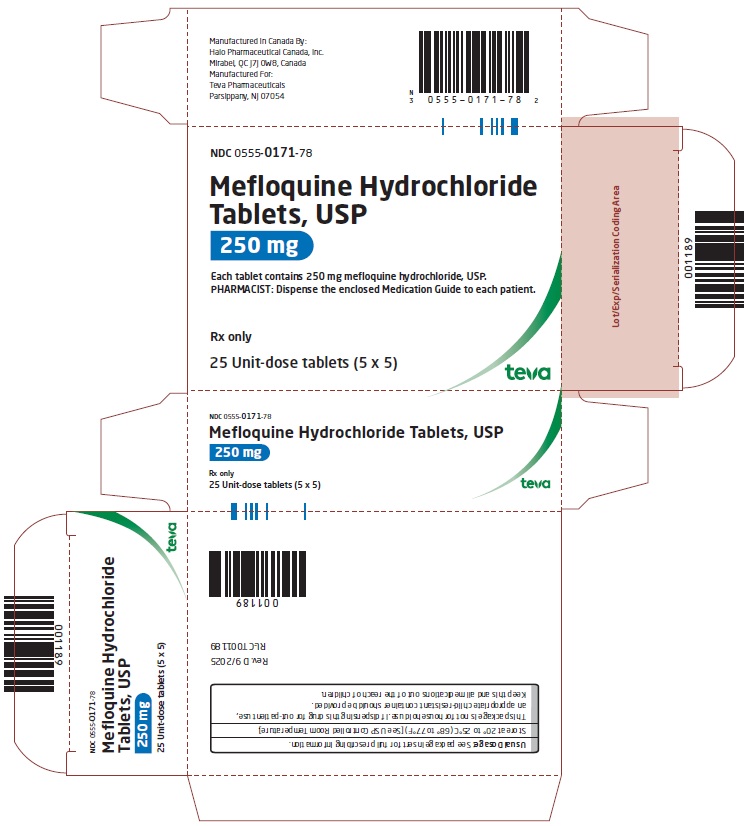 DRUG LABEL: Mefloquine Hydrochloride
NDC: 0555-0171 | Form: TABLET
Manufacturer: Teva Pharmaceuticals USA, Inc.
Category: prescription | Type: HUMAN PRESCRIPTION DRUG LABEL
Date: 20250926

ACTIVE INGREDIENTS: MEFLOQUINE HYDROCHLORIDE 250 mg/1 1
INACTIVE INGREDIENTS: SILICON DIOXIDE; STARCH, CORN; CROSPOVIDONE (15 MPA.S AT 5%); LACTOSE MONOHYDRATE; MAGNESIUM STEARATE; CELLULOSE, MICROCRYSTALLINE; POLOXAMER 188; TALC

Mefloquine Hydrochloride Tablets, USP

Rx only

WARNING

Mefloquine may cause neuropsychiatric adverse reactions that can persist after mefloquine has been discontinued.

Mefloquine should not be prescribed for prophylaxis in patients with major psychiatric disorders. During prophylactic use, if psychiatric or neurologic symptoms occur, the drug should be discontinued and an alternative medication should be substituted (see WARNINGS).

DESCRIPTION

Mefloquine hydrochloride tablets, USP are an antimalarial agent available as 250 mg tablets of mefloquine hydrochloride (equivalent to 228 mg of the free base) for oral administration.

Mefloquine hydrochloride, USP is a 4-quinolinemethanol derivative with the specific chemical name of (R*, S*)-(±)-α-2-piperidinyl-2,8-bis (trifluoromethyl)-4-quinolinemethanol hydrochloride. It is a 2-aryl substituted chemical structural analog of quinine. The drug is a white to almost white crystalline compound, slightly soluble in water. The structural formula is as follows:

C17H16F6N2O.HCl M.W.: 414.78

The inactive ingredients are colloidal silicon dioxide, corn starch, crospovidone, lactose monohydrate, magnesium stearate, microcrystalline cellulose, pregelatinized starch, poloxamer and talc.

FDA approved dissolution test specifications differ from USP.

CLINICAL PHARMACOLOGY

Pharmacokinetics

Absorption: The absolute oral bioavailability of mefloquine has not been determined since an intravenous formulation is not available. The bioavailability of the tablet formation compared with an oral solution was over 85%. The presence of food significantly enhances the rate and extent of absorption, leading to about a 40% increase in bioavailability. In healthy volunteers, plasma concentrations peak 6 to 24 hours (median, about 17 hours) after a single dose of mefloquine. In a similar group of volunteers, maximum plasma concentrations in mcg/L are roughly equivalent to the dose in milligrams (for example, a single 1000 mg dose produces a maximum concentration of about 1000 mcg/L). In healthy volunteers, a dose of 250 mg once weekly produces maximum steady-state plasma concentrations of 1000 to 2000 mcg/L, which are reached after 7 to 10 weeks.

Distribution: In healthy adults, the apparent volume of distribution is approximately 20 L/kg, indicating extensive tissue distribution. Mefloquine may accumulate in parasitized erythrocytes. Experiments conducted in vitro with human blood using concentrations between 50 and 1000 mg/mL showed a relatively constant erythrocyte-to-plasma concentration ratio of about 2 to 1. The equilibrium reached in less than 30 minutes was found to be reversible. Protein binding is about 98%.

Mefloquine crosses the placenta. Excretion into breast milk appears to be minimal (see PRECAUTIONS, Nursing Mothers).

Metabolism: Mefloquine is extensively metabolized in the liver by the cytochrome P450 system. In vitro and in vivo studies strongly suggested that CYP3A4 is the major isoform involved.

Two metabolites of mefloquine have been identified in humans. The main metabolite, 2,8-bis-trifluoromethyl-4-quinoline carboxylic acid, is inactive in Plasmodium falciparum. In a study in healthy volunteers, the carboxylic acid metabolite appeared in plasma 2 to 4 hours after a single oral dose. Maximum plasma concentrations of the metabolite, which were about 50% higher than those of mefloquine, were reached after 2 weeks. Thereafter, plasma levels of the main metabolite and mefloquine declined at a similar rate. The area under the plasma concentration-time curve (AUC) of the main metabolite was 3 to 5 times larger than that of the parent drug. The other metabolite, an alcohol, was present in minute quantities only.

Elimination: In several studies in healthy adults, the mean elimination half-life of mefloquine varied between 2 and 4 weeks, with an average of about 3 weeks. Total clearance, which is essentially hepatic, is in the order of 30 mL/min. There is evidence that mefloquine is excreted mainly in the bile and feces. In volunteers, urinary excretion of unchanged mefloquine and its main metabolite under steady-state condition accounted for about 9% and 4% of the dose, respectively. Concentrations of other metabolites could not be measured in the urine.

Pharmacokinetics in Special Clinical Situations: Children and the Elderly: No relevant age-related changes have been observed in the pharmacokinetics of mefloquine. Therefore, the dosage for children has been extrapolated from the recommended adult dose.

No pharmacokinetic studies have been performed in patients with renal insufficiency since only a small proportion of the drug is eliminated renally. Mefloquine and its main metabolite are not appreciably removed by hemodialysis. No special chemoprophylactic dosage adjustments are indicated for dialysis patients to achieve concentrations in plasma similar to those in healthy persons.

Although clearance of mefloquine may increase in late pregnancy, in general, pregnancy has no clinically relevant effect on the pharmacokinetics of mefloquine.

The pharmacokinetics of mefloquine may be altered in acute malaria.

Pharmacokinetic differences have been observed between various ethnic populations. In practice, however, these are of minor importance compared with host immune status and sensitivity of the parasite.

During long-term prophylaxis (>2 years), the trough concentrations and the elimination half-life of mefloquine were similar to those obtained in the same population after 6 months of drug use, which is when they reached steady-state.

In vitro and in vivo studies showed no hemolysis associated with glucose-6-phosphate dehydrogenase deficiency (see ANIMAL TOXICOLOGY).

Microbiology

Mechanism of Action: Mefloquine is an antimalarial agent which acts as a blood schizonticide. Its exact mechanism of action is not known.

Activity In Vitro and In Vivo: Mefloquine is active against the erythrocytic stages of Plasmodium species (see INDICATIONS AND USAGE). However, the drug has no effect against the exoerythrocytic (hepatic) stages of the parasite. Mefloquine is effective against malaria parasites resistant to chloroquine (see INDICATIONS AND USAGE).

Drug Resistance: Strains of P. falciparum with decreased susceptibility to mefloquine can be selected in vitro or in vivo. Resistance of P. falciparum to mefloquine has been reported in areas of multi-drug resistance in South East Asia. Increased incidences of resistance have also been reported in other parts of the world.

Cross-Resistance: Cross-resistance between mefloquine and halofantrine and cross-resistance between mefloquine and quinine have been observed in some regions.

INDICATIONS AND USAGE

Treatment of Acute Malaria Infections

Mefloquine hydrochloride tablets are indicated for the treatment of mild to moderate acute malaria caused by mefloquine-susceptible strains of P. falciparum (both chloroquine-susceptible and resistant strains) or by Plasmodium vivax. There are insufficient clinical data to document the effect of mefloquine in malaria caused by P. ovale or P. malariae.

Note: Patients with acute P. vivax malaria, treated with mefloquine, are at high risk of relapse because mefloquine does not eliminate exoerythrocytic (hepatic phase) parasites. To avoid relapse, after initial treatment of the acute infection with mefloquine, patients should subsequently be treated with an 8-aminoquinoline derivative (e.g., primaquine).

Prevention of Malaria

Mefloquine hydrochloride tablets are indicated for the prophylaxis of P. falciparum and P. vivax malaria infections, including prophylaxis of chloroquine-resistant strains of P. falciparum.

CONTRAINDICATIONS

Use of mefloquine hydrochloride tablets is contraindicated in patients with a known hypersensitivity to mefloquine or related compounds (e.g., quinine and quinidine) or to any of the excipients contained in the formulation. Mefloquine hydrochloride tablets should not be prescribed for prophylaxis in patients with active depression, a recent history of depression, generalized anxiety disorder, psychosis, schizophrenia or other major psychiatric disorders, or with a history of convulsions.

WARNINGS

In case of life-threatening, serious or overwhelming malaria infections due to P. falciparum, patients should be treated with an intravenous antimalarial drug. Following completion of intravenous treatment, mefloquine may be given to complete the course of therapy.

QTc Interval Prolongation and Drug Interactions

Halofantrine should not be administered with mefloquine or within 15 weeks of the last dose of mefloquine due to the risk of a potentially fatal prolongation of the QTc interval (see CLINICAL PHARMACOLOGY, Pharmacokinetics, Elimination).

Ketoconazole should not be administered with mefloquine or within 15 weeks of the last dose of mefloquine due to the risk of a potentially fatal prolongation of the QTc interval. Ketoconazole increases plasma concentrations and elimination half-life of mefloquine following coadministration (see CLINICAL PHARMACOLOGY, Pharmacokinetics, Elimination and PRECAUTIONS, Drug Interactions).

Concomitant administration of mefloquine and quinine or quinidine may produce electrocardiographic abnormalities.

Psychiatric and Neurologic Adverse Reactions

Mefloquine may cause neuropsychiatric adverse reactions in adults and children. Neuropsychiatric symptoms can be difficult to identify in children. Therefore, vigilance is required to monitor for the occurrence of these symptoms, especially in nonverbal children.

Psychiatric Adverse Reactions

Psychiatric symptoms ranging from anxiety, paranoia, and depression to hallucinations and psychotic behavior can occur with mefloquine use. Symptoms may occur early in the course of mefloquine use. In some cases, these symptoms have been reported to continue for months or years after mefloquine has been stopped. Cases of suicidal ideation and suicide have been reported.

Mefloquine should not be prescribed for prophylaxis in patients with active depression, generalized anxiety disorder, psychosis, or schizophrenia or other major psychiatric disorders. Mefloquine should be used with caution in patients with a previous history of depression.

During prophylactic use, the occurrence of psychiatric symptoms such as acute anxiety, depression, restlessness or confusion suggest a risk for more serious psychiatric disturbances or neurologic adverse reactions. In these cases, the drug should be discontinued and an alternative medication should be substituted.

Neurologic Adverse Reactions

Neurologic symptoms such as dizziness or vertigo, tinnitus, and loss of balance have been reported. These adverse reactions may occur early in the course of mefloquine use and in some cases have been reported to continue for months or years after mefloquine has been stopped. Dizziness or vertigo, tinnitus, and loss of balance have been reported to be permanent in some cases. During prophylactic use, if neurologic symptoms occur, the drug should be discontinued and an alternative medication should be substituted.

Caution should be exercised with regard to activities requiring alertness and fine motor coordination, such as driving, piloting aircraft, operating machinery, and deep-sea diving, while symptoms persist.

Mefloquine may increase the risk of convulsions in patients with epilepsy. The drug should therefore be prescribed only for curative treatment in such patients and only if there are compelling medical reasons for its use (see PRECAUTIONS: Drug Interactions).

Concomitant administration of mefloquine and quinine or chloroquine may increase the risk of convulsions.

Ocular Effects

Eye disorders, including but not limited to optic neuropathy and retinal disorders, have been reported during treatment with mefloquine. Any patient presenting with visual symptoms should be referred to the treating physician and an ophthalmologist as certain conditions (such as retinal disorders or optic neuropathy) may require stopping treatment with mefloquine (see PRECAUTIONS, ANIMAL TOXICOLOGY).

PRECAUTIONS

Hypersensitivity Reactions

Hypersensitivity reactions have been reported with mefloquine use.

Use in Patients with Hepatic Impairment

In patients with impaired liver function the elimination of mefloquine may be prolonged, leading to higher plasma levels and a higher risk of adverse reactions.

Long-Term Use

This drug has been administered for longer than one year. If the drug is to be administered for a prolonged period, periodic evaluations including liver function tests and evaluations for neuropsychiatric effects should be performed (see WARNINGS and ADVERSE REACTIONS, Postmarketing). Periodic ophthalmic examinations are recommended (see WARNINGS).

Cardiac Effects

Parenteral studies in animals show that mefloquine, a myocardial depressant, possesses 20% of the anti-fibrillatory action of quinidine and produces 50% of the increase in the PR interval reported with quinine. The effect of mefloquine on the compromised cardiovascular system has not been evaluated. However, transitory and clinically silent ECG alterations have been reported during the use of mefloquine; alterations included sinus bradycardia, sinus arrhythmia, first degree AV-block, prolongation of the QTc interval and abnormal T waves (see also cardiovascular effects under PRECAUTIONS, Drug Interactions and ADVERSE REACTIONS). The benefits of mefloquine therapy should be weighed against the possibility of adverse effects in patients with cardiac disease.

Drug Resistance and Cross-Resistance

Geographical drug resistance patterns of P. falciparum occur and the preferred choice of malaria prophylaxis might be different from one area to another. For example, resistance of P. falciparum to mefloquine has been reported, predominantly in areas of multi-drug resistance in South-East Asia. Cross-resistance between mefloquine and halofantrine and cross-resistance between mefloquine and quinine have been observed in some regions.

Agranulocytosis and Aplastic Anemia

Cases of agranulocytosis and aplastic anemia have been reported (see ADVERSE REACTIONS).

Laboratory Tests

Periodic evaluation of hepatic function should be performed during prolonged prophylaxis.

Information for Patients

Medication Guide: As required by law, a mefloquine hydrochloride tablets Medication Guide is supplied to patients when mefloquine is dispensed. An information wallet card is also supplied to patients when mefloquine is dispensed. Patients should be instructed to read the Medication Guide when mefloquine is received and to carry the information wallet card with them when they are taking mefloquine. The complete texts of the Medication Guide and information wallet card are reprinted at the end of this document.

Patients should be advised:

- that malaria can be a life-threatening infection
- that mefloquine hydrochloride tablets are being prescribed to help prevent or treat this serious infection;
- that some patients are unable to take this medication because of side effects, including dizziness or vertigo and loss of balance, and it may be necessary to change medications. In some patients it has been reported that these symptoms may continue for months or years after discontinuation of the drug and can be permanent in some cases;
- that insomnia may occur
- that when used as prophylaxis, the first dose of mefloquine hydrochloride tablets should be taken one week prior to arrival in an endemic area;
- that if the patients experience psychiatric adverse reactions such as acute anxiety, depression, restlessness or confusion, or suicidal ideation, the drug should be discontinued and an alternative medication should be substituted;
- that no chemoprophylactic regimen is 100% effective, and protective clothing, insect repellents, and bed nets are important components of malaria prophylaxis;
- to seek medical attention for any febrile illness that occurs after return from a malaria area and to inform their physician that they may have been exposed to malaria.

Drug Interactions

Drug-drug interactions with mefloquine have not been explored in detail. There is one report of cardiopulmonary arrest, with full recovery, in a patient who was taking a beta blocker (propranolol) (see PRECAUTIONS, Cardiac Effects). The effects of mefloquine on the compromised cardiovascular system have not been evaluated. The benefits of mefloquine therapy should be weighed against the possibility of adverse effects in patients with cardiac disease.

Halofantrine

Halofantrine should not be administered with mefloquine or within 15 weeks of the last dose of mefloquine due to the risk of a potentially fatal prolongation of the QTc interval (see WARNINGS).

Other Antimalarial Drugs

Concomitant administration of mefloquine and other related antimalarial compounds (e.g., quinine, quinidine and chloroquine) may produce electrocardiographic abnormalities and increase the risk of convulsions (see WARNINGS). If these drugs are to be used in the initial treatment of severe malaria, mefloquine administration should be delayed at least 12 hours after the last dose. Clinically significant QTc prolongation has not been found with mefloquine alone.

Ketoconazole (Potent Inhibitor of CYP3A4)

Coadministration of a single 500 mg oral dose of mefloquine with 400 mg of ketoconazole once daily for 10 days in 8 healthy volunteers resulted in an increase in the mean Cmax and AUC of mefloquine by 64% and 79%, respectively, and an increase in the mean elimination half-life of mefloquine from 322 hours to 448 hours. Ketoconazole should not be administered with mefloquine or within 15 weeks of the last dose of mefloquine due to the risk of a potentially fatal prolongation of the QTc interval (see WARNINGS).

Other Drugs that Prolong the QTc Interval

Coadministration of other drugs known to alter cardiac conduction (e.g., anti-arrhythmic or beta-adrenergic blocking agents, calcium channel blockers, antihistamines or H1-blocking agents, tricyclic antidepressants and phenothiazines) might also contribute to a prolongation of the QTc interval. There are no data that conclusively establish whether the concomitant administration of mefloquine and the above listed agents has an effect on cardiac function.

Anticonvulsants

In patients taking an anticonvulsant (e.g., valproic acid, carbamazepine, phenobarbital or phenytoin), the concomitant use of mefloquine may reduce seizure control by lowering the plasma levels of the anticonvulsant. Therefore, patients concurrently taking anti-seizure medication and mefloquine should have the blood level of their anti-seizure medication monitored and the dosage adjusted appropriately (see PRECAUTIONS).

Vaccines

When mefloquine is taken concurrently with oral live typhoid vaccines, attenuation of immunization cannot be excluded. Vaccinations with attenuated live bacteria should therefore be completed at least 3 days before the first dose of mefloquine hydrochloride tablets.

Rifampin (Potent Inducer of CYP3A4)

Coadministration of a single 500 mg oral dose of mefloquine and 600 mg of rifampin once daily for 7 days in 7 healthy Thai volunteers resulted in a decrease in the mean Cmax and AUC of mefloquine by 19% and 68%, respectively, and a decrease in the mean elimination half-life of mefloquine from 305 hours to 113 hours. Rifampin should be used cautiously in patients taking mefloquine.

Inhibitors and Inducers of CYP3A4

Mefloquine does not inhibit or induce the CYP 450 enzyme system. Thus, concomitant administration of mefloquine hydrochloride tablets and substrates of the CYP 450 enzyme system is not expected to result in a drug interaction. However, mefloquine is metabolized by CYP3A4 and inhibitors of CYP3A4 may modify the pharmacokinetics/metabolism of mefloquine, leading to an increase in mefloquine plasma concentrations and potential risk of adverse reactions. Therefore, mefloquine hydrochloride tablets should be used with caution when administered concomitantly with CYP3A4 inhibitors. Similarly, inducers of CYP3A4 may modify the pharmacokinetics/metabolism of mefloquine, leading to a decrease in mefloquine plasma concentrations and potential reduction in efficacy of mefloquine hydrochloride tablets. Therefore, mefloquine hydrochloride tablets should also be used with caution when administered concomitantly with CYP3A4 inducers.

Substrates and Inhibitors of P-glycoprotein

It has been shown in vitro that mefloquine is a substrate and an inhibitor of P-glycoprotein. Therefore, drug-drug interactions could also occur with drugs that are substrates or are known to modify the expression of this transporter. The clinical relevance of these interactions is not known to date.

Other Potential Interactions

No other drug interactions are known. Nevertheless, the effects of mefloquine on travelers receiving concomitant medications, particularly diabetics or patients using anticoagulants, should be checked before departure.

In clinical trials, the concomitant administration of sulfadoxine and pyrimethamine did not alter the adverse reaction profile of mefloquine.

Carcinogenesis, Mutagenesis, Impairment of Fertility

Carcinogenesis: The carcinogenic potential of mefloquine was studied in rats and mice in 2-year feeding studies at doses of up to 30 mg/kg/day. No treatment-related increases in tumors of any type were noted.

Mutagenesis: The mutagenic potential of mefloquine was studied in a variety of assay systems including: Ames test, a host-mediated assay in mice, fluctuation tests and a mouse micronucleus assay. Several of these assays were performed with and without prior metabolic activation. In no instance was evidence obtained for the mutagenicity of mefloquine.

Impairment of Fertility: Fertility studies in rats at doses of 5, 20, and 50 mg/kg/day of mefloquine have demonstrated adverse effects on fertility in the male at the high dose of 50 mg/kg/day, and in the female at doses of 20 and 50 mg/kg/day. Histopathological lesions were noted in the epididymides from male rats at doses of 20 and 50 mg/kg/day. Administration of 250 mg/week of mefloquine (base) in adult males for 22 weeks failed to reveal any deleterious effects on human spermatozoa.

Teratogenic Effects

Pregnancy Category B

Data from published studies in pregnant women have shown no increase in the risk of teratogenic effects or adverse pregnancy outcomes following mefloquine treatment or prophylaxis during pregnancy. Reproduction studies in mice, rats and rabbits have shown teratogenic effects at doses similar to the clinical acute treatment dose in humans. Because the studies in humans cannot rule out the possibility of harm, mefloquine should be used during pregnancy only if clearly needed.

Published data on mefloquine use during pregnancy include randomized controlled trials, intervention trials, prospective and retrospective cohort studies, and case series. These data showed that pregnant women who took mefloquine at various doses for both prevention and treatment of malaria did not have an increased risk of teratogenic effects or adverse pregnancy outcomes compared to the background rate in the general population. These data include more than 700 exposures to mefloquine in the first trimester of pregnancy and over 2,000 exposures in the second and third trimester.

Mefloquine administered to pregnant mice, rats, and rabbits was teratogenic at doses similar to the clinical acute treatment dose of 21 to 25 mg/kg, based on body surface area comparisons. In all three animal species, CNS effects (e.g., exencephaly, hydrocephaly or partially missing medulla oblongata) and craniofacial malformations were observed. At the same doses, mefloquine was also embryotoxic in mice and rabbits. All of these findings were observed at doses that were maternally toxic.

Nursing Mothers

Mefloquine is excreted in human milk in small amounts, the activity of which is unknown. Based on a study in a few subjects, low concentrations (3% to 4%) of mefloquine were excreted in human milk following a dose equivalent to 250 mg of the free base. Caution should be exercised when administered to a nursing woman.

Pediatric Use

Use of mefloquine to treat acute, uncomplicated P. falciparum malaria in pediatric patients is supported by evidence from adequate and well-controlled studies of mefloquine in adults with additional data from published open-label and comparative trials using mefloquine to treat malaria caused by P. falciparum in patients younger than 16 years of age. The safety and effectiveness of mefloquine for the treatment of malaria in pediatric patients below the age of 6 months have not been established.

In several studies, the administration of mefloquine for the treatment of malaria was associated with early vomiting in pediatric patients. Early vomiting was cited in some reports as a possible cause of treatment failure. If a second dose is not tolerated, the patient should be monitored closely and alternative malaria treatment considered if improvement is not observed within a reasonable period of time (see WARNINGS and DOSAGE AND ADMINISTRATION).

Geriatric Use

Clinical studies of mefloquine did not include sufficient numbers of subjects aged 65 and older to determine whether they respond differently from younger subjects. Other reported clinical experience has not identified differences in responses between the elderly and younger patients. Since electrocardiographic abnormalities have been observed in individuals treated with mefloquine (see PRECAUTIONS) and underlying cardiac disease is more prevalent in elderly than in younger patients, the benefits of mefloquine therapy should be weighed against the possibility of adverse cardiac effects in elderly patients.

ADVERSE REACTIONS

Clinical

At the doses used for treatment of acute malaria infections, the symptoms possibly attributable to drug administration cannot be distinguished from those symptoms usually attributable to the disease itself.

Among subjects who received mefloquine for prophylaxis of malaria, the most frequently observed adverse experience was vomiting (3%). Dizziness, syncope, extrasystoles and other complaints affecting less than 1% were also reported.

Two serious adverse reactions were cardiopulmonary arrest in one patient shortly after ingesting a single prophylactic dose of mefloquine while concomitantly using propranolol (see PRECAUTIONS, Drug Interactions), and encephalopathy of unknown etiology during prophylactic mefloquine administration. The relationship of encephalopathy to drug administration could not be clearly established.

Among subjects who received mefloquine for treatment, the most frequently observed adverse experiences included: dizziness, myalgia, nausea, fever, headache, vomiting, chills, diarrhea, skin rash, abdominal pain, fatigue, loss of appetite, and tinnitus. Those side effects occurring in less than 1% included bradycardia, hair loss, emotional problems, pruritus, asthenia, transient emotional disturbances and telogen effluvium (loss of resting hair). Seizures have also been reported.

Laboratory

The most frequently observed laboratory alterations which could be possibly attributable to drug administration were decreased hematocrit, transient elevation of transaminases, leukopenia and thrombocytopenia. These alterations were observed in patients with acute malaria who received treatment doses of the drug and were attributed to the disease itself.

During prophylactic administration of mefloquine to indigenous populations in malaria-endemic areas, the following alterations in laboratory values were observed: transient elevation of transaminases, leukocytosis or thrombocytopenia.

Because of the long half-life of mefloquine, adverse reactions to mefloquine may occur or persist up to several weeks after discontinuation of the drug.

Postmarketing

Postmarketing surveillance indicates that the same kind of adverse reactions are reported during prophylaxis, as well as acute treatment. Because these adverse reactions are reported voluntarily from a population of uncertain size, it is not always possible to reliably estimate their frequency or establish a causal relationship to mefloquine exposure.

The most frequently reported adverse reactions are nausea, vomiting, loose stools or diarrhea, abdominal pain, dizziness or vertigo, loss of balance, and neuropsychiatric events such as headache, somnolence, and sleep disorders (insomnia, abnormal dreams). These adverse reactions may occur early in the course of mefloquine use. It has been reported that dizziness or vertigo, tinnitus and hearing impairment, and loss of balance may continue for months or years after discontinuation of the drug and may be permanent in some cases.

More severe neuropsychiatric disorders have been reported such as: sensory and motor neuropathies (including paresthesia, tremor and ataxia), convulsions, agitation or restlessness, anxiety, depression, mood swings, panic attacks, memory impairment, confusion, hallucinations, aggression, psychotic or paranoid reactions and encephalopathy. Cases of suicidal ideation and suicide have been reported.

Other less frequently reported adverse reactions include:

Cardiovascular Disorders: circulatory disturbances (hypotension, hypertension, flushing, syncope), chest pain, tachycardia or palpitation, bradycardia, irregular heart rate, extrasystoles, A-V block, and other transient cardiac conduction alterations.

Skin Disorders: rash, exanthema, erythema, urticaria, pruritus, edema, hair loss, erythema multiforme, and Stevens-Johnson syndrome.

Musculoskeletal Disorders: muscle weakness, muscle cramps, myalgia, and arthralgia.

Respiratory Disorders: dyspnea, pneumonitis of possible allergic etiology.

Hepatobiliary Disorders: drug-related hepatic disorders from asymptomatic transient transaminase elevations to hepatic failure.

Blood and Lymphatic System Disorders: agranulocytosis, aplastic anemia.

Ocular Disorders: visual impairment, vision blurred, cataracts, retinal disorders, optic neuropathy.

Other Symptoms: asthenia, malaise, fatigue, fever, hyperhidrosis, chills, dyspepsia and loss of appetite.

To report SUSPECTED ADVERSE REACTIONS, contact Teva at 1-888-838-2872 or FDA at 1-800-FDA-1088 or www.fda.gov/medwatch.

OVERDOSAGE

Symptoms and Signs

In cases of overdosage with mefloquine, the symptoms mentioned under ADVERSE REACTIONS may be more pronounced.

Treatment

Patients should be managed by symptomatic and supportive care following mefloquine overdose. There are no specific antidotes. Monitor cardiac function (if possible by ECG) and neuropsychiatric status. Provide symptomatic and intensive supportive treatment as required.

DOSAGE AND ADMINISTRATION

Malaria Treatment in Adults

Treatment of mild to moderate malaria in adults caused by mefloquine-susceptible strains of P. falciparum or by P. vivax: Dosage: Five tablets (1250 mg) mefloquine hydrochloride to be given as a single oral dose. The drug should not be taken on an empty stomach and should be administered with at least 8 oz (240 mL) of water.

If a full-treatment course with mefloquine does not lead to improvement within 48 to 72 hours, mefloquine should not be used for retreatment. An alternative therapy should be used. Similarly, if previous prophylaxis with mefloquine failed, mefloquine should not be used for curative treatment (see INDICATIONS AND USAGE).

Note: Patients with acute P. vivax malaria, treated with mefloquine, are at high risk of relapse because mefloquine does not eliminate exoerythrocytic (hepatic phase) parasites. To avoid relapse after initial treatment of the acute infection with mefloquine, patients should subsequently be treated with an 8-aminoquinoline derivative (e.g., primaquine).

Malaria Prophylaxis in Adults

Dosage: One 250 mg mefloquine hydrochloride tablet once weekly.

Prophylactic drug administration should begin 1 week before arrival in an endemic area. Subsequent weekly doses should be taken regularly, always on the same day of each week, preferably after the main meal. To reduce the risk of malaria after leaving an endemic area, prophylaxis must be continued for 4 additional weeks to ensure suppressive blood levels of the drug when merozoites emerge from the liver. Tablets should not be taken on an empty stomach and should be administered with at least 8 oz (240 mL) of water.

In certain cases, e.g., when a traveler is taking other medication, it may be desirable to start prophylaxis 2 to 3 weeks prior to departure, in order to ensure that the combination of drugs is well tolerated (see PRECAUTIONS, Drug Interactions).

When prophylaxis with mefloquine fails, physicians should carefully evaluate which antimalarial to use for therapy.

Malaria Treatment in Pediatric Patients

Treatment of mild to moderate malaria in pediatric patients caused by mefloquine-susceptible strains of P. falciparum: Dosage: 20 to 25 mg/kg body weight. Splitting the total therapeutic dose into 2 doses taken 6 to 8 hours apart may reduce the occurrence or severity of adverse effects. The pediatric dose should not exceed the adult dose.

Experience with mefloquine in pediatric patients weighing less than 20 kg is limited.

The drug should not be taken on an empty stomach and should be administered with ample water. The tablets may be crushed and suspended in a small amount of water, milk or other beverage for administration to small children and other persons unable to swallow them whole.

If a full-treatment course with mefloquine does not lead to improvement within 48 to 72 hours, mefloquine should not be used for retreatment. An alternative therapy should be used. Similarly, if previous prophylaxis with mefloquine has failed, mefloquine should not be used for curative treatment.

In pediatric patients, the administration of mefloquine for the treatment of malaria has been associated with early vomiting. In some cases, early vomiting has been cited as a possible cause of treatment failure (see PRECAUTIONS). If a significant loss of drug product is observed or suspected because of vomiting, a second full dose of mefloquine should be administered to patients who vomit less than 30 minutes after receiving the drug. If vomiting occurs 30 to 60 minutes after a dose, an additional half-dose should be given. If vomiting recurs, the patient should be monitored closely and alternative malaria treatment considered if improvement is not observed within a reasonable period of time.

The safety and effectiveness of mefloquine to treat malaria in pediatric patients below the age of 6 months have not been established.

Malaria Prophylaxis in Pediatric Patients

The recommended prophylactic dose of mefloquine is approximately 5 mg/kg body weight once weekly. One 250 mg mefloquine hydrochloride tablet should be taken once weekly in pediatric patients weighing over 45 kg. In pediatric patients weighing less than 45 kg, the weekly dose decreases in proportion to body weight:

30 to 45 kg: 3/4 tablet

20 to 30 kg: 1/2 tablet

Experience with mefloquine in pediatric patients weighing less than 20 kg is limited.

HOW SUPPLIED

Mefloquine hydrochloride tablets USP, 250 mg are available as white, oval-shaped, flat-faced, beveled-edge, scored tablets, debossed with “stylized b” 171 on the scored side and plain on the other side, packaged in unit-dose cartons of 25 tablets (NDC 0555-0171-78).

Store at 20° to 25°C (68° to 77°F) [see USP Controlled Room Temperature].

Keep this and all medications out of the reach of children.

ANIMAL TOXICOLOGY

Ocular lesions were observed in rats fed mefloquine daily for 2 years. All surviving rats given 30 mg/kg/day had ocular lesions in both eyes characterized by retinal degeneration, opacity of the lens, and retinal edema. Similar but less severe lesions were observed in 80% of female and 22% of male rats fed 12.5 mg/kg/day for 2 years. At doses of 5 mg/kg/day, only corneal lesions were observed. They occurred in 9% of rats studied.

Male Wistar rats orally administered-mefloquine daily for 22 days at the equivalent human therapeutic plasma concentration showed CNS penetration of mefloquine, with a 30 to 50 fold greater brain/plasma drug ratio up to 10 days after the final dose administered.^1

REFERENCES

1. Baudry S., Pham YT., Baune B., Vidrequin S., Crevoisier CH., Gimenez F., Fainotti R. (1997). Stereoselective passage of mefloquine through the blood brain barrier in the rat. J. Pharm. Pharmacol. 49: 1086-1090.

Brands listed are the trademarks of their respective owners.

Manufactured In Canada By:
Halo Pharmaceutical Canada, Inc.
Mirabel, QC J7J 0W8, Canada

Manufactured For:
Teva Pharmaceuticals
Parsippany, NJ 07054

Rev. F 9/2025

MEDICATION GUIDE

Mefloquine Hydrochloride (mef' loe kwin hye" droe klor' ide) Tablets, USP

Important:

Your doctor or pharmacist will give you an Information Wallet Card along with this

Medication Guide. It has important information about mefloquine hydrochloride tablets and should be carried with

you at all times while you take mefloquine hydrochloride tablets.

What is the most important information I should know about mefloquine hydrochloride tablets?

Mefloquine hydrochloride tablets can cause serious side effects, including:

1. Heart Problems.

Do not take halofantrine (used to treat malaria) or ketoconazole (used for fungal infections) with

mefloquine hydrochloride tablets or within 15 weeks of your last dose of mefloquine hydrochloride tablets. You may get serious heart

problems (problems with the electrical system of your heart called QT prolongation) that can lead

to death. Do not take quinine (Qualaquin®) or quinidine (used to treat malaria or irregular heart

beat) with mefloquine hydrochloride tablets. You may get serious heart problems.

2. Mental problems. Symptoms of serious mental problems may include:

- severe anxiety
- paranoia (feelings of mistrust towards others)
- hallucinations (seeing or hearing things that are not there)
- depression
- feeling restless
- unusual behavior
- feeling confused

Some people who take mefloquine hydrochloride tablets think about suicide (putting an end to their life). Some people who were taking mefloquine hydrochloride tablets committed suicide. It is not known if mefloquine hydrochloride tablets was responsible for those suicides.

If you have any of these serious mental problems, or you develop other serious side effects or mental problems, you should contact your doctor right away as it may be necessary to stop taking mefloquine hydrochloride tablets and use a different medicine to prevent malaria.

3. Problems with your body’s nervous system. Symptoms of serious nervous system

problems may include:

- dizziness
- a feeling that you or things around you are moving or spinning (vertigo)
- loss of balance
- ringing sound in your ears (tinnitus)
- convulsions (seizures) in people who already have seizures (epilepsy)
- convulsions (seizures) in people who take quinine or chloroquine (used to treat malaria) with mefloquine hydrochloride tablets. Do not take quinine (Qualaquin®) or chloroquine (Aralen®) with mefloquine hydrochloride tablets.
- unable to sleep (insomnia)

Dizziness, vertigo, tinnitus, and loss of balance can go on for months or years after

mefloquine hydrochloride tablets are stopped or may become permanent in some people.

Important:

You need to take malaria prevention medicine before you travel to a malaria area, while

you are in a malaria area, and after you return from a malaria area.

- If you are told by a doctor to stop taking mefloquine hydrochloride tablets because of the side effects or for other reasons, you will need to take different malaria medicine.
- If you do not have access to a doctor or to another medicine and have to stop taking mefloquine hydrochloride tablets, leave the malaria area and contact a doctor as soon as possible because leaving the malaria area may not protect you from getting malaria. You will still need to take malaria prevention medicine for another 4 weeks after you leave the malaria area.

What is mefloquine hydrochloride tablets?

Mefloquine hydrochloride tablets is a prescription medicine used to prevent and treat malaria. Malaria can be a life-threatening infection. Mefloquine hydrochloride tablets does not work for all types of malaria.

It is not known if mefloquine hydrochloride tablets is safe and effective in children under 6 months old for the treatment of malaria. It is not known how well mefloquine hydrochloride tablets works to prevent malaria in children weighing less than 44 pounds (20 kilograms).

Who should not take mefloquine hydrochloride tablets?

Do not take mefloquine hydrochloride tablets if you have:

- depression or had depression recently
- had recent mental problems, including anxiety disorder, schizophrenia, or psychosis (losing touch with reality)
- seizures or had seizures (epilepsy or convulsions)
- an allergy to quinine, quinidine, mefloquine or any ingredients in mefloquine hydrochloride tablets. See the end of this Medication Guide for a complete list of ingredients in mefloquine hydrochloride tablets.

Talk to your doctor before you take mefloquine hydrochloride tablets if you have any of the medical conditions listed above.

What should I tell my doctor before taking mefloquine hydrochloride tablets?

Before taking mefloquine hydrochloride tablets, tell your doctor about all your medical conditions, including if you have:

- heart disease
- liver problems
- seizures or epilepsy
- diabetes
- blood clotting problems or take blood thinner medicines (anticoagulants)
- mental problems
- are pregnant or plan to become pregnant. It is not known if mefloquine hydrochloride tablets will harm your unborn baby. Talk to your doctor if you are pregnant or plan to become pregnant.
- You should use birth control while you take mefloquine hydrochloride tablets and for 3 months after you stop mefloquine hydrochloride tablets. If you have an unplanned pregnancy, talk to your doctor right away.
- are breastfeeding or plan to breastfeed. Mefloquine hydrochloride tablets can pass into your breast milk and may harm your baby. Ask your doctor if you will need to stop breastfeeding or use a different medicine.

Contact your doctor right away if you have a fever after leaving a malaria area.

Tell your doctor about all the medicines you take, including prescription and nonprescription medicines, vitamins, and herbal supplements. Mefloquine hydrochloride tablets and other medicines may affect each other causing side effects.

How should I take mefloquine hydrochloride tablets?

- Take mefloquine hydrochloride tablets exactly as your doctor tells you to take it. Your doctor will tell you how many mefloquine hydrochloride tablets to take and when to take them.
- You will start taking mefloquine hydrochloride tablets to prevent malaria between 1 to 3 weeks before you travel to a malaria area.
- Take mefloquine hydrochloride tablets just after eating your largest meal of the day and with at least 1 cup (8 ounces) of water.
- Do not take mefloquine hydrochloride tablets on an empty stomach.
- If you vomit after taking mefloquine hydrochloride tablets, contact your doctor to see if you should take another dose.
- Continue taking mefloquine hydrochloride tablets for 4 weeks after returning from a malaria area.
- Mefloquine hydrochloride tablets may be crushed and mixed with a small amount of water, milk or other beverage for children or other people unable to swallow mefloquine hydrochloride tablets whole. Your doctor will tell you the correct dose for your child based on your child’s weight.
- If you take mefloquine hydrochloride tablets for a year or longer, your doctor should check your:
  - eyes (especially if you have trouble seeing while you take mefloquine hydrochloride tablets)
  - liver function (to see if there has been damage to your liver)
- Use protective clothing, insect repellents, and bed nets to protect you from being bitten by mosquitoes. Medicine alone does not always stop you from catching malaria from mosquito bites.

What should I avoid while taking mefloquine hydrochloride tablets?

Avoid activities such as driving a car or using heavy machinery or other activities needing alertness and careful movements (fine motor coordination) until you know how mefloquine hydrochloride tablets affects you. You may feel dizzy or lose your balance. This could happen for months or years after you stop taking mefloquine hydrochloride tablets and can be permanent in some cases. See “What are the possible side effects of mefloquine hydrochloride tablets?”

What are the possible side effects of mefloquine hydrochloride tablets?

See “What is the most important information I should know about mefloquine hydrochloride tablets?”

Mefloquine hydrochloride tablets may cause serious side effects, including:

- liver problems

Call your healthcare provider right away if you have unexplained symptoms such as nausea or vomiting, stomach pain, fever, weakness, itching, unusual tiredness, loss of appetite, light colored bowel movements, dark colored urine, yellowing of your skin or the white of your eyes.

The most common side effects of mefloquine hydrochloride tablets include:

- nausea
- vomiting
- diarrhea
- abdominal pain
- headache

The most common side effects in people who take mefloquine hydrochloride tablets for treatment include:

- muscle pain
- fever
- chills
- skin rash
- fatigue
- loss of appetite
- irregular heart beat

Tell your doctor if you have any side effect that bothers you or that does not go away. These are not all the possible side effects of mefloquine hydrochloride tablets. For more information, ask your doctor or pharmacist.

Call your doctor for medical advice about side effects. You may report side effects to FDA at 1-800-FDA-1088.

How should I store mefloquine hydrochloride tablets?

- Store mefloquine hydrochloride tablets between 20º to 25ºC (68º to 77ºF)
- Safely throw away medicine that is out of date or no longer needed.

Keep mefloquine hydrochloride tablets and all medicines out of the reach of children.

General information about the safe and effective use of mefloquine hydrochloride tablets.

Medicines are sometimes prescribed for purposes other than those listed in a Medication Guide. Do not use mefloquine hydrochloride tablets for a condition for which it was not prescribed. Do not give mefloquine hydrochloride tablets to other people, even if they have the same symptoms that you have. It may harm them.

This Medication Guide summarizes the most important information about mefloquine hydrochloride tablets. If you would like more information, talk with your doctor. You can ask your pharmacist or doctor for information about mefloquine hydrochloride tablets that is written for health professionals.

What are the ingredients in mefloquine hydrochloride tablets?

Active ingredient: mefloquine hydrochloride

Inactive ingredients: colloidal silicon dioxide, corn starch, crospovidone, lactose monohydrate, magnesium stearate, microcrystalline cellulose, pregelatinized starch, poloxamer and talc.

Brands listed are the trademarks of their respective owners.

This Medication Guide has been approved by the U.S. Food and Drug Administration.

Manufactured In Canada By:
Halo Pharmaceutical Canada, Inc.
Mirabel, QC J7J 0W8, Canada

Manufactured For:
Teva Pharmaceuticals
Parsippany, NJ 07054

Rev. E 9/2025

Information Wallet Card

Mefloquine Hydrochloride (mef' loe kwin hye" droe klor' ide) Tablets, USP

It is important that you read the entire Medication Guide for additional information on mefloquine hydrochloride tablets.

Carry this wallet card with you when you are taking mefloquine hydrochloride tablets.

Important: You need to take malaria prevention medicine before you travel to a malaria area, while you are in a malaria area, and after you return from a malaria area.

Mefloquine hydrochloride tablets can cause serious side effects,

including:

1. Heart problems.

Do not take halofantrine (used to treat malaria) or ketoconazole (used for fungal infections) with mefloquine hydrochloride tablets or within 15 weeks of your last dose of mefloquine hydrochloride tablets. You may get serious heart problems that can lead to death. Do not take quinine (Qualaquin®) or quinidine (used to treat malaria or irregular heart beat) with mefloquine hydrochloride tablets. You may get serious heart problems. Mefloquine hydrochloride tablets may cause serious problems with the electrical system of your heart, called QT prolongation.

2. Mental problems. Symptoms of serious mental problems may include severe anxiety, paranoia (feelings of mistrust towards others), hallucinations (seeing or hearing things that are not there), depression, feeling restless, unusual behavior or feeling confused. Some people who take mefloquine hydrochloride tablets think about suicide (putting an end to their life). Some people who were taking mefloquine hydrochloride tablets committed suicide. It is not known if mefloquine hydrochloride tablets was responsible for those suicides.

If you have any of these serious mental problems you should contact your doctor right away as it may be necessary to stop taking mefloquine hydrochloride tablets and use a different medicine to prevent malaria.

3. Problems with your body’s nervous system.

Do not take quinine (Qualaquin®) or chloroquine (Aralen®) (used to treat malaria) with mefloquine hydrochloride tablets. You may have a greater risk for convulsions (seizures).

Symptoms of serious nervous system problems may include dizziness, a feeling that you or things around you are moving or spinning (vertigo), loss of balance, ringing in your ears (tinnitus), convulsions (seizures) in people who already have seizures, or you are unable to sleep (insomnia).

These serious mental and nervous system side effects can go on for months or years after mefloquine hydrochloride tablets is stopped or may become

permanent in some people.

If you are told by a doctor to stop taking mefloquine hydrochloride tablets because of the side effects or for other reasons, you will need to take a different malaria medicine.

If you do not have access to a doctor or to a different medicine and have to stop taking mefloquine hydrochloride tablets, leave the malaria area and contact a doctor as soon as possible because leaving the malaria area may not protect you from getting malaria. You will still need to take a malaria prevention medicine for another 4 weeks after you leave the malaria area.

Mefloquine hydrochloride tablets may cause serious liver problems.

Symptoms of liver problems include nausea, vomiting, loss of appetite, unusual tiredness, stomach pain, fever, weakness, itching, light-colored bowel movements, dark colored urine, yellowing of your skin or the white of your eyes. The most common side effects of mefloquine hydrochloride tablets include nausea, vomiting, diarrhea, abdominal pain and headache.

Tell your doctor if you have any side effect that bothers you or that does not go away. These are not all the possible side effects of mefloquine hydrochloride tablets. For more information, ask your doctor or pharmacist.

Call your doctor for medical advice about side

effects. You may report side effects to FDA at 1-800-FDA-1088.

What should I avoid while taking mefloquine hydrochloride tablets?

Avoid activities such as driving a car or using heavy machinery or other activities needing alertness and careful movements (fine motor coordination) until you know how mefloquine hydrochloride tablets affects you. You may feel dizzy or lose your balance. This could happen for months or years after you stop taking mefloquine hydrochloride tablets and can be permanent in some cases.

Brands listed are the trademarks of their respective owners.

Manufactured In Canada By: Halo Pharmaceutical Canada, Inc., Mirabel, QC J7J 0W8, Canada

Manufactured For: Teva Pharmaceuticals, Parsippany, NJ 07054

Rev. E 9/2025

PRINCIPAL DISPLAY PANEL

NDC 0555-0171-78
Mefloquine Hydrochloride Tablets, USP
250 mg
Each tablet contains 250 mg mefloquine hydrochloride, USP.
PHARMACIST: Dispense the enclosed Medication Guide to each patient.
Rx only
25 Unit-dose tablets (5 x 5)